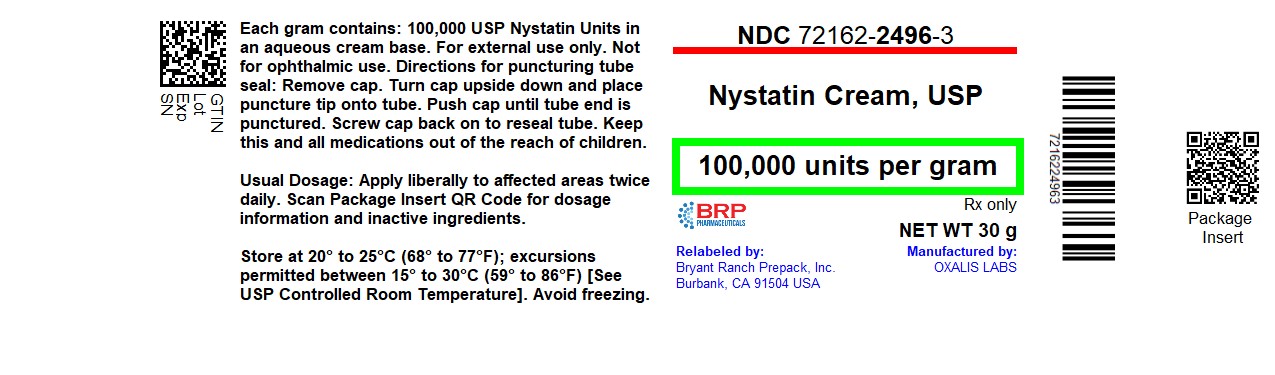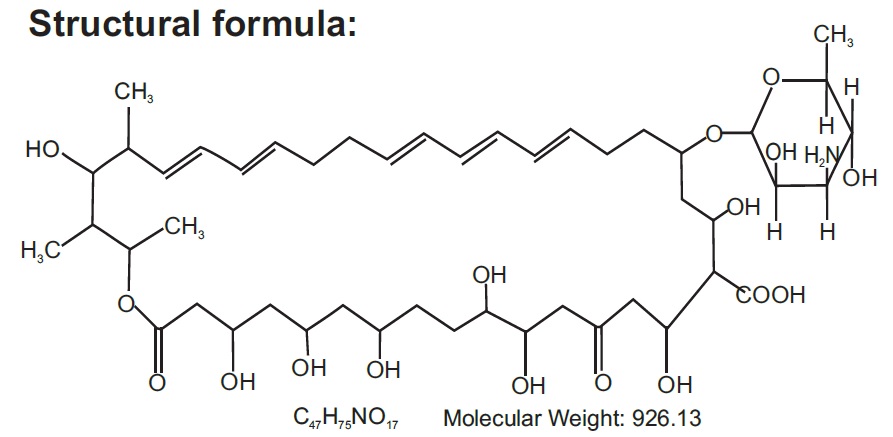 DRUG LABEL: Nystatin
NDC: 72162-2496 | Form: CREAM
Manufacturer: Bryant Ranch Prepack
Category: prescription | Type: HUMAN PRESCRIPTION DRUG LABEL
Date: 20251008

ACTIVE INGREDIENTS: NYSTATIN 100000 [USP'U]/1 g
INACTIVE INGREDIENTS: PETROLATUM; ALUMINUM HYDROXIDE; TITANIUM DIOXIDE; CETEARETH-15; PROPYLENE GLYCOL; PROPYLPARABEN; POLYETHYLENE GLYCOL 400; GLYCERYL MONOSTEARATE; METHYLPARABEN; SORBITOL

Nystatin Cream,USP, 100,000 units per gram
Rx only
FOR TOPICAL USE ONLY • NOT FOR OPHTHALMIC USE

DESCRIPTION

Nystatin is a polyene antifungal antibiotic obtained from Streptomyces nursei.

Nystatin cream is for dermatologic use.
Nystatin cream for topical use, contains 100,000 USP Nystatin Units in an aqueous cream base containing aluminium hydroxide, ceteareth-15, polyethylene glycol monostearate, glycerol monostearate, propylene glycol, purified water, simethicone emulsion, non-crystallizing sorbitol solution, titanium dioxide, white petrolatum with methyl paraben and propyl paraben as preservatives.

CLINICAL PHARMACOLOGY

Pharmacokinetics
Nystatin is not absorbed from intact skin or mucous membrane.
Microbiology
Nystatin is an antibiotic which is both fungistatic and fungicidal in vitro against a wide variety of yeasts and yeast-like fungi, including Candida albicans, C. parapsilosis, C. tropicalis, C. guilliermondi, C. pseudotropicalis, C. krusei, Torulopsis glabrata, Tricophyton rubrum, T. mentagrophytes. Nystatin acts by binding to sterols in the cell membrane of susceptible species resulting in a change in membrane permeability and the subsequent leakage of intracellular components. On repeated subculturing with increasing levels of nystatin, Candida albicans does not develop resistance to nystatin. Generally, resistance to nystatin does not develop during therapy. However, other species of Candida (C. tropicalis, C. guilliermondi, C. krusei, and C. stellatoides) become quite resistant on treatment with Nystatin and simultaneously become cross resistant to amphotericin as well. This resistance is lost when the antibiotic is removed. Nystatin exhibits no appreciable activity against bacteria, protozoa, or viruses.

INDICATIONS & USAGE

Nystatin cream is indicated in the treatment of cutaneous or mucocutaneous mycotic infections caused by Candida albicans and other susceptible Candida species.
This cream is not indicated for systemic, oral, intravaginal or ophthalmic use.

CONTRAINDICATIONS

Nystatin cream is contraindicated in patients with a history of hypersensitivity to any of its components.

PRECAUTIONS

GENERAL PRECAUTIONS

Nystatin cream should not be used for the treatment of systemic, oral, intravaginal or ophthalmic infections.

If irritation or sensitization develops, treatment should be discontinued and appropriate measures taken as indicated. It is recommended that KOH smears, cultures, or other diagnostic methods be used to confirm the diagnosis of cutaneous or mucocutaneous candidiasis and to rule out infection caused by other pathogens.

INFORMATION FOR PATIENTS

Patients using this medication should receive the following information and instructions:

1. The patient should be instructed to use this medication as directed (including the replacement of missed doses). This medication is not for any disorder other than that for which it is prescribed.
2. Even if symptomatic relief occurs within the first few days of treatment, the patient should be advised not to interrupt or discontinue therapy until the prescribed course of treatment is completed.

If symptoms of irritation develop, the patient should be advised to notify the physician promptly.

LABORATORY TESTS

If there is a lack of therapeutic response, KOH smears, cultures, or other diagnostic methods should be repeated.

CARCINOGENESIS & MUTAGENESIS & IMPAIRMENT OF FERTILITY

No long-term animal studies have been performed to evaluate the carcinogenic potential of nystatin. No studies have been performed to determine the mutagenicity of nystatin or the effects on male or female fertility.

PREGNANCY

Teratogenic Effects
Animal reproduction studies have not been conducted with any nystatin cream. It also is not known whether this cream can cause fetal harm when used by a pregnant woman or can affect reproductive capacity. Nystatin cream should be prescribed for a pregnant woman only if the potential benefit to the mother outweighs the potential risk to the fetus.

NURSING MOTHERS

It is not known whether nystatin is excreted in human milk. Caution should be exercised when nystatin is prescribed for a nursing woman.

PEDIATRIC USE

Safety and effectiveness have been established in the pediatric population from birth to 16 years.

(See DOSAGE AND ADMINISTRATION.)

GERIATRIC USE

Clinical studies with nystatin cream did not include sufficient numbers of subjects aged 65 years and older to determine whether they respond differently than younger subjects. Other reported clinical experience has not identified differences in responses between elderly and younger patients, but greater sensitivity of some older individuals cannot be ruled out.

ADVERSE REACTIONS

The frequency of adverse events reported in patients using nystatin cream is less than 0.1%. The more common events that were reported include allergic reactions, burning, itching, rash, eczema, and pain on application. (See PRECAUTIONS: General.)

DOSAGE & ADMINISTRATION

Adults and Pediatric Patients (Neonates and Older)
Apply liberally to affected areas twice daily or as indicated until healing is complete.

HOW SUPPLIED

Nystatin Cream USP is a yellow to light green cream. It is supplied as:

15 gram Tube NDC 72162-2496-02

30 gram Tube NDC 72162-2496-03

Store at 20° to 25°C (68° to 77°F); excursions permitted between 15° to 30°C (59° to 86°F) [See USP Controlled Room Temperature]. Avoid freezing.

Repackaged/Relabeled by:
Bryant Ranch Prepack, Inc.
Burbank, CA 91504

PACKAGE LABEL

Nystatin 100,000 units/g Cream #15